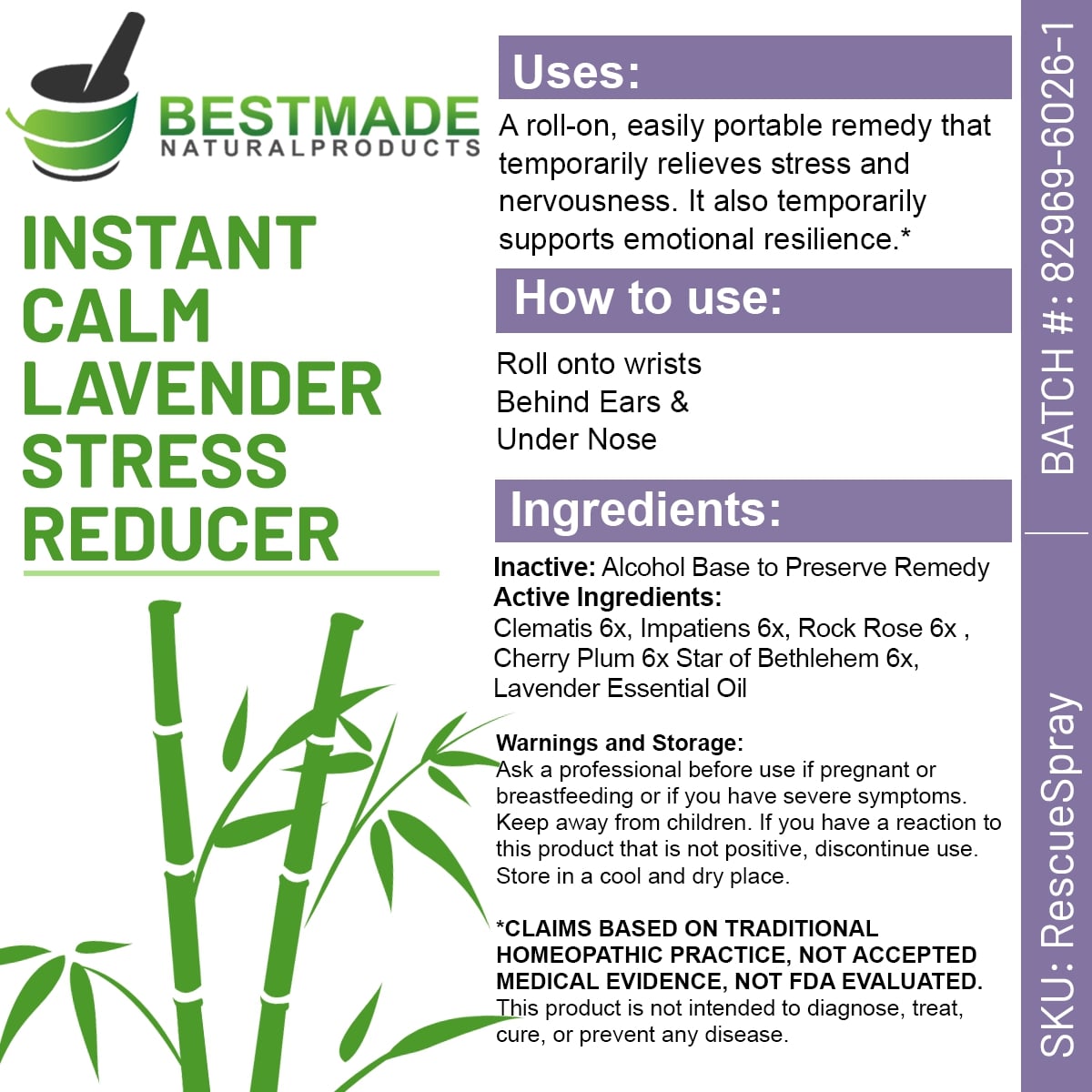 DRUG LABEL: Bestmade Natural Products Instant Calm Lavender Stress Reducer
NDC: 82969-6026 | Form: LIQUID
Manufacturer: Bestmade Natural Products
Category: homeopathic | Type: HUMAN OTC DRUG LABEL
Date: 20250314

ACTIVE INGREDIENTS: ORNITHOGALUM UMBELLATUM FLOWERING TOP 6 [hp_X]/6 [hp_X]; IMPATIENS GLANDULIFERA FLOWER 6 [hp_X]/6 [hp_X]; CLEMATIS VITALBA FLOWER 6 [hp_X]/6 [hp_X]; LAVENDER OIL 6 [hp_X]/6 [hp_X]; HELIANTHEMUM NUMMULARIUM FLOWER 6 [hp_X]/6 [hp_X]; PRUNUS CERASIFERA FLOWER 6 [hp_X]/6 [hp_X]
INACTIVE INGREDIENTS: ALCOHOL 6 [hp_X]/6 [hp_X]

INSTANT CALM LAVENDER STRESS REDUCER

DOSAGE AND ADMINISTRATION

How to use:

Roll onto wrists

Behind Ears & Under Nose

Inactive:

Alcohol Base to Preserve Product

Uses:

A roll-on, easily portable remedy that temporarily relieves stress and nervousness. It also temporarily supports emotional resilience.*

*CLAIMS BASED ON TRADITIONAL HOMEOPATHIC PRACTICE, NOT ACCEPTED MEDICAL EVIDENCE, NOT FDA EVALUATED.

This product is not intended to diagnose, treat, cure, or prevent any disease.

Uses:

A roll-on, easily portable remedy that temporarily relieves stress and nervousness. It also temporarily supports emotional resilience.*

*CLAIMS BASED ON TRADITIONAL HOMEOPATHIC PRACTICE, NOT ACCEPTED MEDICAL EVIDENCE, NOT FDA EVALUATED.

This product is not intended to diagnose, treat, cure, or prevent any disease.

Active Ingredients:
Clematis 6x, Impatiens 6x, Rock Rose 6x, Cherry Plum 6x Star of Bethlehem 6x, Lavender Essential Oil

KEEP OUT OF REACH OF CHILDREN

Warnings and Storage:

Ask a professional before use if pregnant or breastfeeding or if you have severe symptoms. Keep away from children. If you have a reaction to this product that is not positive, discontinue use. Store in a cool and dry place.

Warnings and Storage:

Ask a professional before use if pregnant or breastfeeding or if you have severe symptoms. Keep away from children. If you have a reaction to this product that is not positive, discontinue use. Store in a cool and dry place.

*CLAIMS BASED ON TRADITIONAL HOMEOPATHIC PRACTICE, NOT ACCEPTED MEDICAL EVIDENCE NOT FDA EVALUATED.

This product is not intended to diagnose, treat, cure, or prevent any disease.

Entire package label